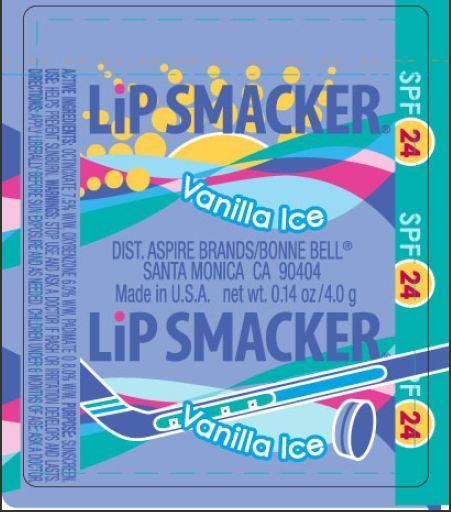 DRUG LABEL: Lip Smacker SPF 24 Vanilla Ice
                
NDC: 50051-0017 | Form: LIPSTICK
Manufacturer: Bonne Bell LLC
Category: otc | Type: HUMAN OTC DRUG LABEL
Date: 20121016

ACTIVE INGREDIENTS: OCTINOXATE 7.5 g/100 g; OXYBENZONE 6 g/100 g; PADIMATE O 8 g/100 g
INACTIVE INGREDIENTS: RICINUS COMMUNIS SEED; CETYL ACETATE; YELLOW WAX; CANDELILLA WAX; CARNAUBA WAX; ACETYLATED LANOLIN ALCOHOLS; SESAME OIL; ISOPROPYL MYRISTATE; PARAFFIN; WHEAT GERM OIL; MICA; PROPYLENE GLYCOL; STEARIC ACID; PROPYL GALLATE; CITRIC ACID MONOHYDRATE; NEOTAME; TITANIUM DIOXIDE; D&C RED NO. 28; D&C RED NO. 22

Lip Smacker SPF 24 Vanilla Ice

ACTIVE INGREDIENTS

OCTINOXATE 7.5% W/W, OXYBENZONE 6.0% W/W, PADIMATE O 8.0% W/W.

PURPOSE

SUNSCREEN

USE

HELPS PREVENT SUNBURN

WARNINGS

STOP USE AND ASK A DOCTOR IF RASH OR IRRITATION DEVELOPS AND LASTS.

DIRECTIONS

APPLY LIBERALLY BEFORE SUN EXPOSURE AND AS NEEDED.

ASK DOCTOR

CHILDREN UNDER 6 MONTHS OF AGE, ASK A DOCTOR.

PACKAGE LABEL DISPLAY

LiP SMACKER (R)

Vanilla Ice

DIST. ASPIRE BRANDS/BONNE BELL (R)
SANTA MONICA CA 90404
Made in U.S.A. net wt. 0.14 oz/4.0 g

SPF 24